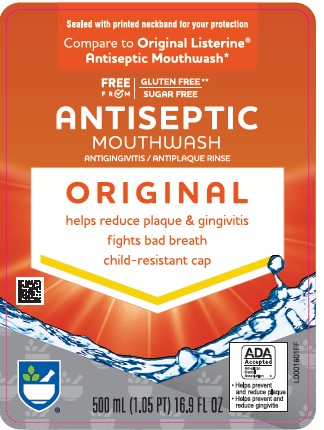 DRUG LABEL: Oral Care Antiseptic
NDC: 11822-3108 | Form: MOUTHWASH
Manufacturer: Rite Aid Corporation
Category: otc | Type: HUMAN OTC DRUG LABEL
Date: 20260130

ACTIVE INGREDIENTS: EUCALYPTOL 0.92 mg/1 mL; MENTHOL 0.42 mg/1 mL; METHYL SALICYLATE 0.6 mg/1 mL; THYMOL 0.64 mg/1 mL
INACTIVE INGREDIENTS: WATER; ALCOHOL; BENZOIC ACID; POLOXAMER 407; SODIUM BENZOATE; CARAMEL

Rite Aid 318.003/318AH-AI
Antiseptic Mouthrinse

Active ingredients

Eucalyptol 0.092%

Menthol 0.042%

Methyl Salicylate 0.060%

Thymol 0.064%

Purpose

Antigingivitis, Antiplaque

Use

helps control plaque that leads to gingivitis

Warnings

For this product

Do not use

if you have painful or swollen gums, pus from the gum line, loose teeth or increased spacing between the teeth. See your dentist immediately. These may be signs of periodontitis, a serious form of gum disease.

Stop use and ask a dentist

gingivitis, bleeding, or redness persists for more than 2 weeks

Keep out of reach of children.

If more than used for rinsing is accidentally swallowed, get medical help or contact a Poison Control Center right away.

Directions

adults and children 12 years of age and older - vigorously swish 20 mL (2/3 FL OZ or 4 teaspoonfuls) between teeth for 30 seconds then spit out; do not swallow
children under 12 years of age - consult a dentist or doctor

- this rinse is not intended to replace brushing or flossing

0ther information

cold weather may cloud this product. Its antiseptic properties are not affected. Store at room temperature (59°-77°F).

Inactive ingredients

water, alcohol 26.9%, benzoic acid, poloxamer 407, sodium benzoate, caramel

Disclaimer

*This product is not manufactured or distributed by Kenvue, Inc., distributor of Original Listerine Antiseptic Mouthwash.

Claims

**While this product has no added gluten, there is no guarantee that this product's ingredients have not been exposed to gluten.

OUR PROMISE:

Gluten Free**

Sugar Free

Adverse Reaction

DISTRIBUTED BY: RITE AID

200 NEWBERRY COMMONS

ETTERS, PA 17319

www.riteaid.com

SATISFACTION GUARANTEE

If you're not satisfied, we'll happily refund your money.

DSP-TN-21091

DSP-MO-20087

Principal display panel

Sealed with printed neckband for your protection

Compare to Original Listerine ® Antiseptic Mouthwash*

FREE FROM

GLUTEN FREE**

SUGAR FREE

ANTISEPTIC

MOUTHWASH

ANTIGINGIVITIS/ANTIPLAQUE RINSE

ORIGINAL

helps reduce plaque & gingivitis

fights bad breath

child-resistant cap

ADA Accepted

American Dental Association

- Helps prevent and reduce plaque
- Hepls prevent and reduce gingivitis

500 mL (1.05 PT) 16.9 FL OZ